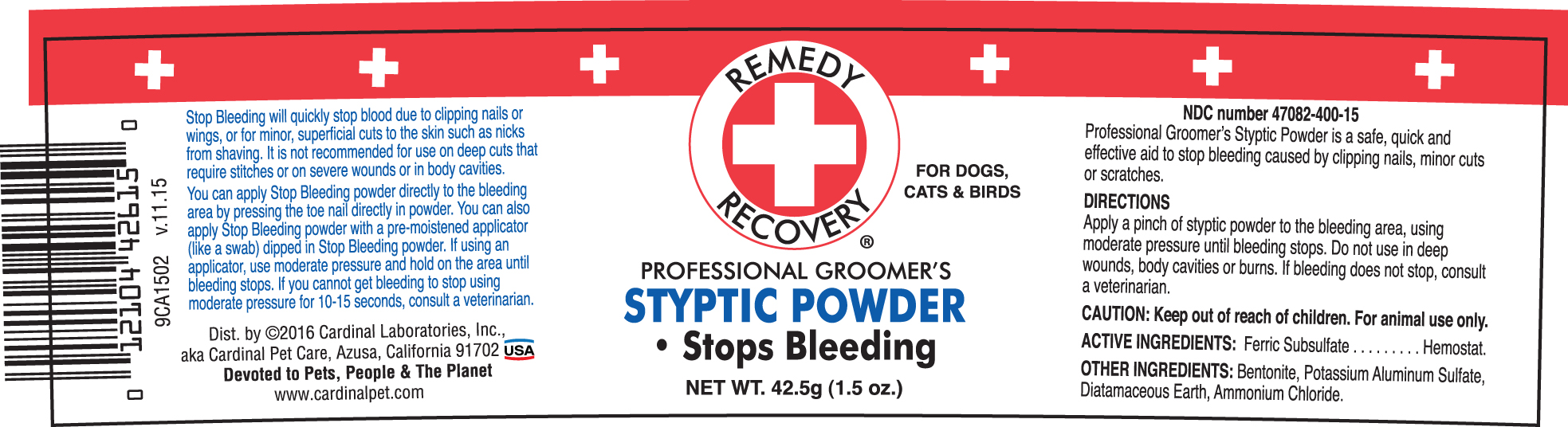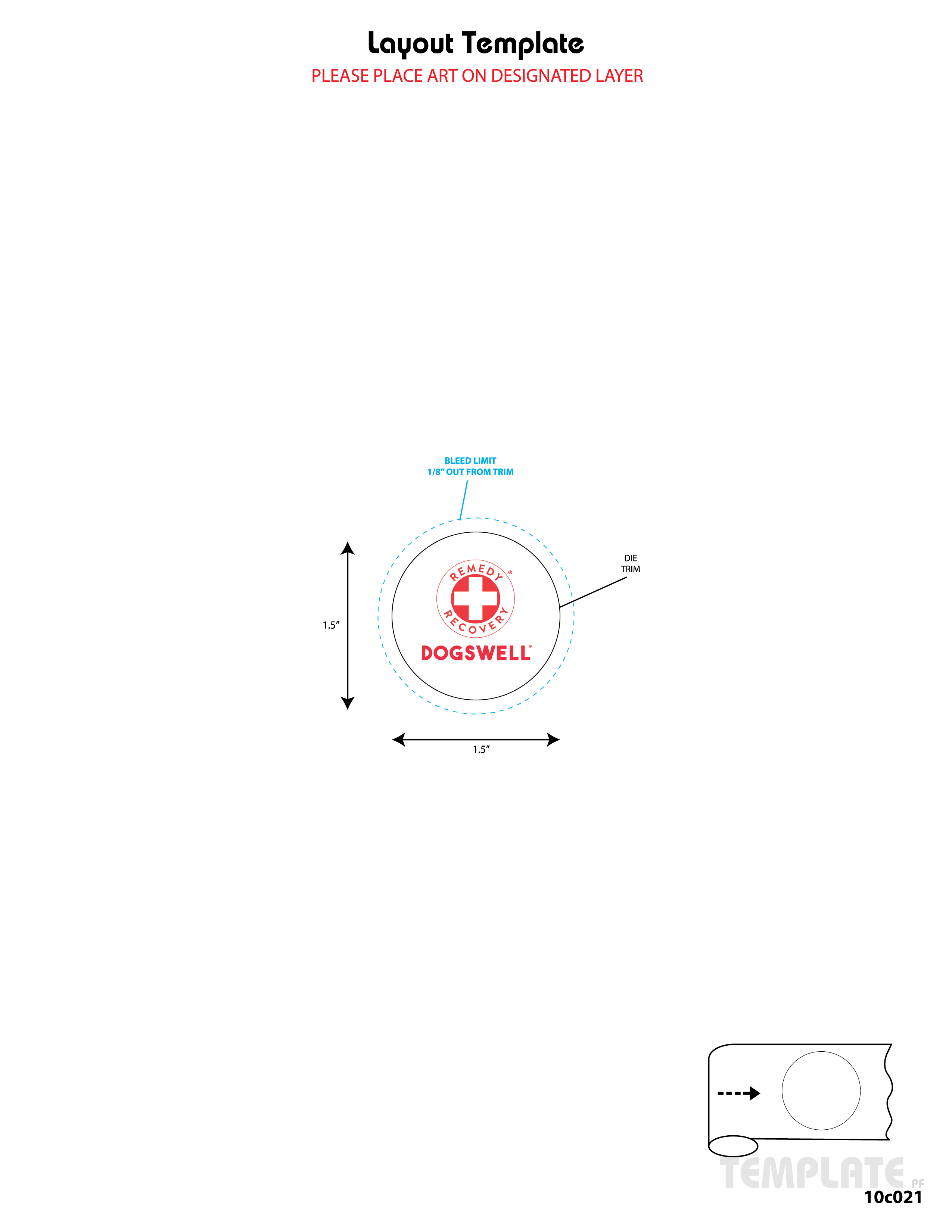 DRUG LABEL: Styptic Powder
NDC: 47082-400 | Form: POWDER
Manufacturer: Westwood Laboratories Inc.
Category: animal | Type: OTC ANIMAL DRUG LABEL
Date: 20211006

ACTIVE INGREDIENTS: FERRIC SUBSULFATE 35 g/100 g
INACTIVE INGREDIENTS: BENTONITE ; POTASSIUM SULFATE; DIATOMACEOUS EARTH; AMMONIUM CHLORIDE

Styptic Powder

ACTIVE INGREDIENTS

Ferric Subsulfate.........Hemostat.

INSTRUCTIONS FOR USE

Professional Groomer's Styptic Powder is a safe, quick and effective aid to stop bleeding caused by clipping nails, minor cuts or scratches.

CAUTION

Keep out of reach of children. For animal use only.

DIRECTIONS

Apply a pinch of styptic powder to the bleeding area, using moderate pressure until bleeding stops. Dont use in deep wounds, bosy cavities, or burns. If bleeding does not stop, consult veterinarian.

OTHER INGREDIENTS

Bentonite, Potassium Aluminum Sulfate, Diatomaceous Earth, Ammonium Chloride.

DESCRIPTION

Stop bleeding will quickly stop blood due to clipping nails or wings, or for minor, superficialcuts to the skin such as nicks from shaving. It is not recommended for use on deep cuts that require stitches or on severe wounds or in body cavities.

You can apply Stop Bleeding powder directly to the bleeding area by pressing the toe nail directly in powder. You can also apply Stop Bleeding powder with a pre-moistened applicator (like a swab) dipped in Stop Bleeding powder. If using an applicator, use moderate pressure and hold on the area until bleeding stops. If you cannot get bleeding to stop using moderate pressure for 10-15 seconds, consult a veterinarian.

Dist. by (c)2016 Cardinal Laboratories, Inc.,

aka Cardinal Pet Care, Azusa, California 91702 USA

Devoted to Pets, People & The Planet

www.cardinalpet.com

Dogswell Remedy & Recovery